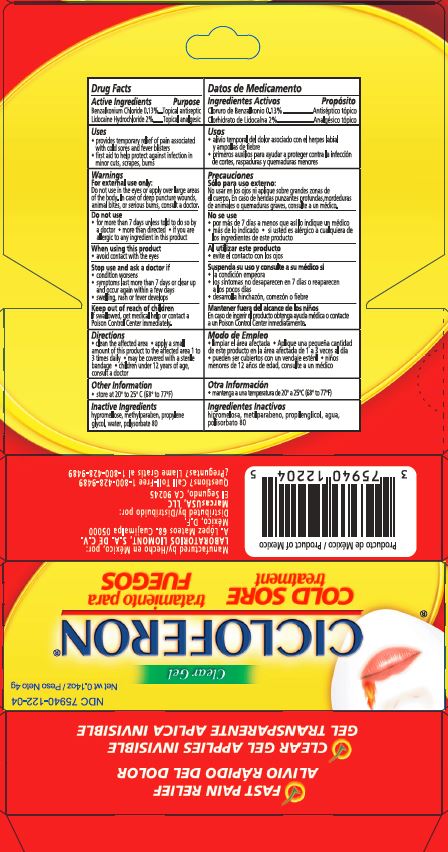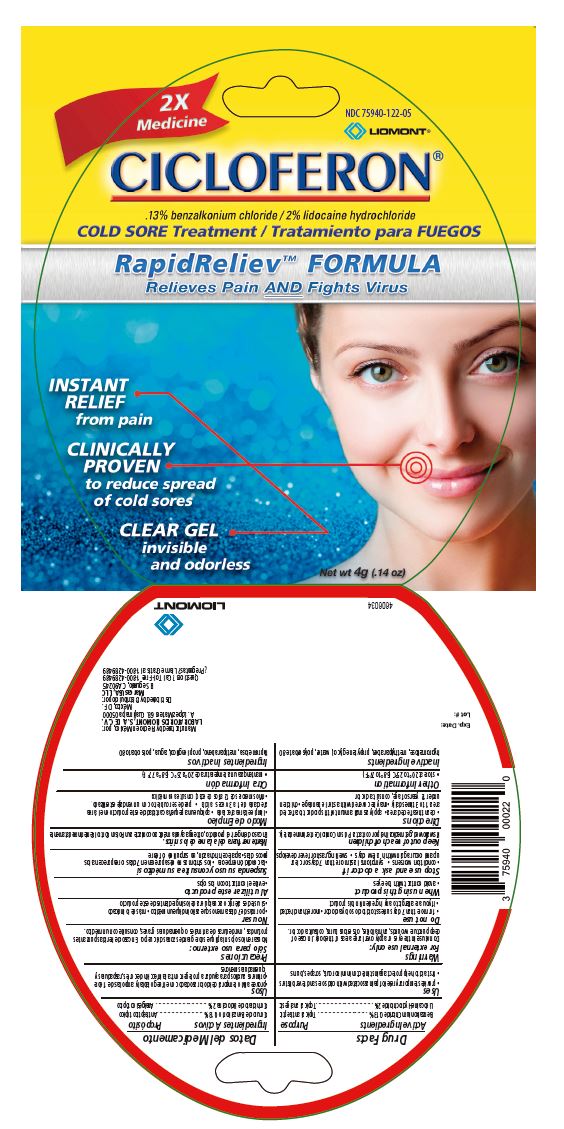 DRUG LABEL: CICLOFERON
NDC: 75940-122 | Form: GEL
Manufacturer: MarcasUSA LLC
Category: otc | Type: HUMAN OTC DRUG LABEL
Date: 20191219

ACTIVE INGREDIENTS: BENZALKONIUM CHLORIDE 1.3 mg/1 g; LIDOCAINE HYDROCHLORIDE 20 mg/1 g
INACTIVE INGREDIENTS: HYPROMELLOSES; METHYLPARABEN; PROPYLENE GLYCOL; WATER; POLYSORBATE 80

Drug Facts

Active ingredients
Benzalkonium Chloride 0.13%
Lidocaine Hydrochloride 2%

Purpose
Topical antiseptic
Topical analgesic

PURPOSE

Uses

- provides temporary relief of pain associated with cold sores and fever blisters
- first aid to help protect against infection in minor cuts, scrapes, burns

Warnings

For external use only

Do not use in the eyes or apply over large areas of the body. In case of deep puncture wounds, animal bites, or serious burns, consult a doctor.

Do not use

- for more than 7 days unless told to do so by a doctor
- more than directed
- if you are allergic to any ingredient in this product

When using this product

- avoid contact with the eyes

Stop use and ask a doctor if

- condition worsens
- symptoms last more than 7 days or clear up and occur again within a few days
- swelling, rash or fever develops

Keep out of reach of children

If swallowed, get medical help or contact a Poison Control Center immediately.

Directions

- clean the affected area
- apply a small amount of this product to the affected area 1 to 3 times daily
- may be covered with a sterile bandage
- children under 12 years of age, consult a doctor

Other Information

store at 20° to 25°C (68° to 77°F)

Inactive Ingredients

hypromellose, methylparaben, propylene glycol, water, polysorbate 80

Manufactured by/Hecho en México por:
LABORATORIOS LIOMONT, S.A. DE C.V.
A. López Mateos 68. Cuajimalpa 05000
México, DF
Distributed by/Distribuido por: MarcasUSA, LLC
El Segundo, CA 90245
Questions? Call Toll-Free 1-800-428-9489
¿Preguntas? Llame Gratis al 1-800-428-9489

ACTIVE INGREDIENT

Ingredientes Activos
Cloruro de Benzalkonio 0.13%
Clorhidrato de Lidocaina 2%

Propósito
Antiséptico tópico
Analgésico tópico

Usos

- alivio temporal del dolor asociado con el herpes labial y ampollas de fiebre
- primeros auxilios para ayudar a proteger contra la infección de cortes, raspaduras y quemaduras menores

Precauciones

Sólo para uso externo:

No usar en los ojos ni aplique sobre grandes zonas de el cuerpo. En caso de heridas punzantes profundas, mordeduras de animales o quemaduras graves, consulte a un médico.

No se use

- por más de 7 días a menos que así lo indique un médico
- más de lo indicado
- si usted es alérgico a cualquiera de los ingredientes de este producto

Al utilizar este producto

- evite el contacto con los ojos

Suspenda su uso y consulte a su médico si

- la condición empeora
- los síntomas no desaparecen en 7 días o reaparecen a los pocos dias
- desarrolla hinchazón, comezón o fiebre

Mantener fuera del alcance de los niños.

En caso de ingerir el producto obtenga ayuda médica o contacte a un Poison Control Center inmediatamente.

Modo de Empleo

- limpiar el área afectada
- Aplique una pequeña cantidad de este producto en la área afectada de 1 a 3 veces al día
- pueden ser cubiertos con un vendaje estéril
- niños menores de 12 años de edad, consulte a un médico

Otra información

mantenga a una temperatura de 20°a 25°C (68° a 77°F)

Ingredientes Inactivos

hipromelosa, metilparabeno, propilenglicol, agua, polisorbato 80

Manufactured by/Hecho en México por:
LABORATORIOS LIOMONT, S.A. DE C.V.
A. López Mateos 68. Cuajimalpa 05000
México, DF
Distributed by/Distribuido por: MarcasUSA, LLC
El Segundo, CA 90245
Questions? Call Toll-Free 1-800-428-9489
¿Preguntas? Llame Gratis al 1-800-428-9489

PRINCIPAL DISPLAY PANEL

FAST PAIN RELIEF
ALIVIO RÁPIDO DEL DOLOR

CLEAR GEL APPLIES INVISIBLE
GEL TRANSPARENTE APLICA INVISIBLE

NDC 75940-122-04

Net wt 0.14oz / Peso Neto 4g

Clear Gel

CICLOFERON®

COLD SORE
treatment

tratamiento para
FUEGOS

Manufactured by/Hecho en México por:
LABORATORIOS LIOMONT, S.A. DE C.V.
A. López Mateos 68. Cuajimalpa 05000
México, DF

Distributed by/Distribuido por:
MarcasUSA, LLC
El Segundo, CA 90245
Questions? Call Toll-Free 1-800-428-9489
¿Preguntas? Llame Gratis al 1-800-428-9489

2X Medicine
Cicloferon

NDC 75940-122-05

LIOMONT

0.13% benzalkonium chloride/2% lidocaine hydrochloride

COLD SORE Treatment / Tatamiento para FUEGOS

RAPIDRELIEVTM FORMULA

Relieves Pain AND Fights Virus

INSTANT RELIEF from Pain

CLINICAL PROVEN to reduce spread of cold sores

CLEAR GEL invisible and odorless

Net wt 4g (.14 oz)